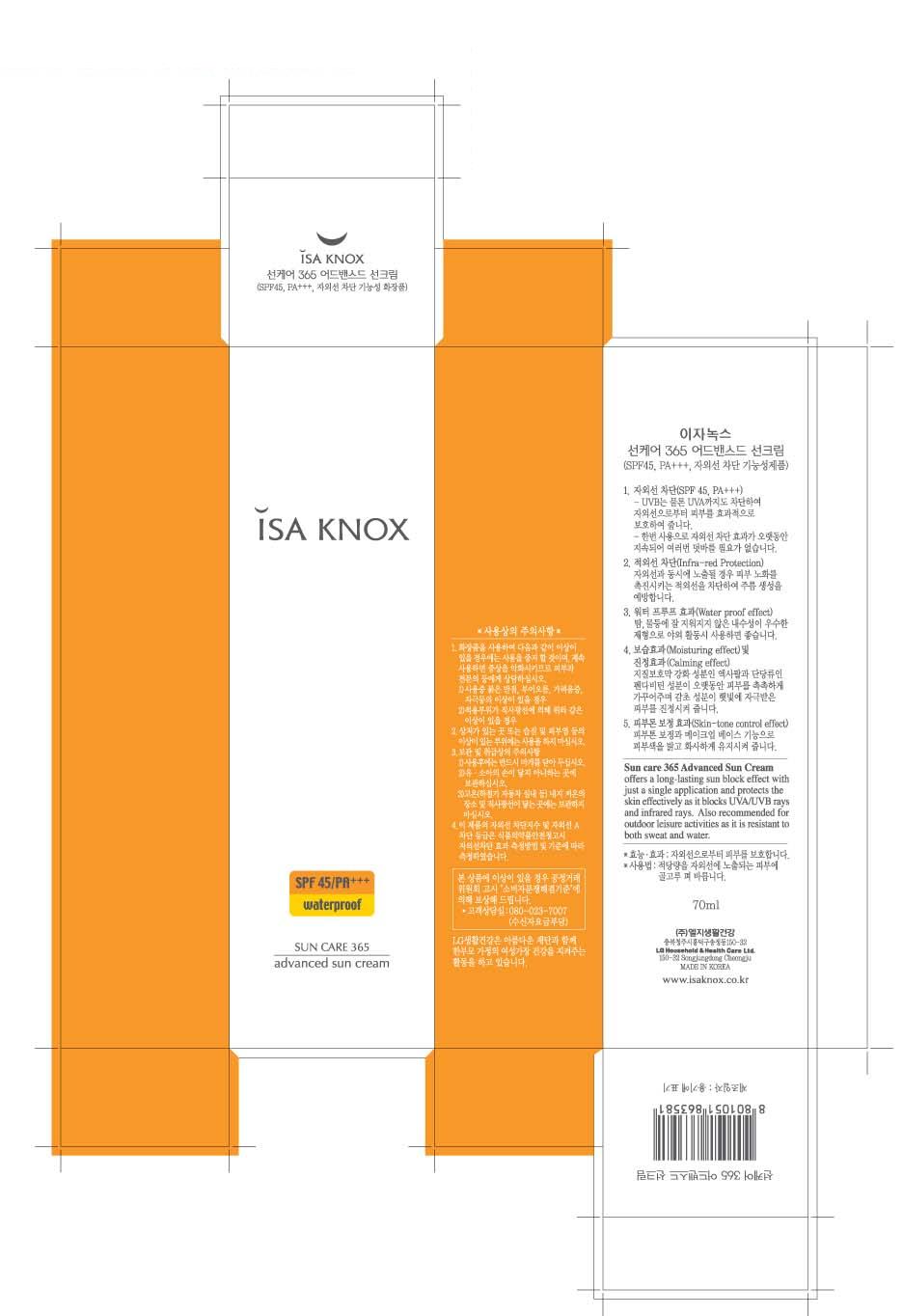 DRUG LABEL: ISAKNOX SUNCARE 365 ADVANCED SUN
NDC: 53208-393 | Form: CREAM
Manufacturer: LG Household and Healthcare, Inc.
Category: otc | Type: HUMAN OTC DRUG LABEL
Date: 20100421

ACTIVE INGREDIENTS: ZINC OXIDE 11 mL/100 mL; OCTINOXATE 7 mL/100 mL; TITANIUM DIOXIDE 1 mL/100 mL
INACTIVE INGREDIENTS: WATER; ZINC OXIDE; BUTYLENE GLYCOL; CYCLOMETHICONE; DIPROPYLENE GLYCOL; DIMETHICONE; MAGNESIUM SULFATE; SORBITAN SESQUIOLEATE; PANTHENOL; METHYLPARABEN; GLYCYRRHIZINATE DIPOTASSIUM; ETHYLPARABEN; CHAMAEMELUM NOBILE FLOWER; ADIPIC ACID; FERRIC OXIDE YELLOW; ALPHA-TOCOPHEROL ACETATE; FERRIC OXIDE RED; FERROSOFERRIC OXIDE

Drug Facts

ACTIVE INGREDIENT

ZINC OXIDE 11.00g/100g

OCTINOXATE 7.00g/100g

TITANIUM DIOXIDE 1.00g/100g

WARNINGS AND PRECAUTIONS

For external use only

Keep out of reach of children. Is swallowed, get medical help or contact a Poison Control Center right away.

WHEN USING

Keep out of eyes. Rinse with water to remove.

Stop use if a rash or irritation develops and lasts.